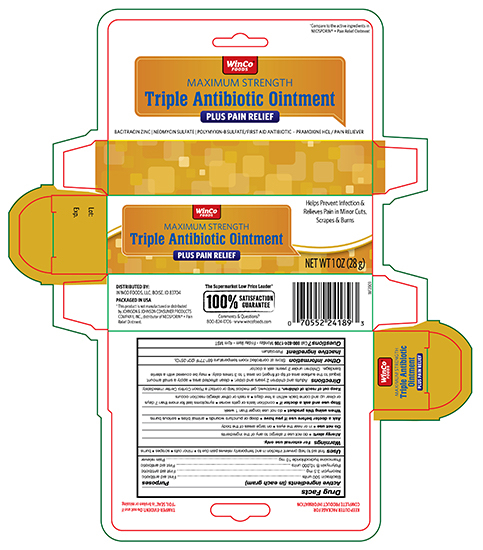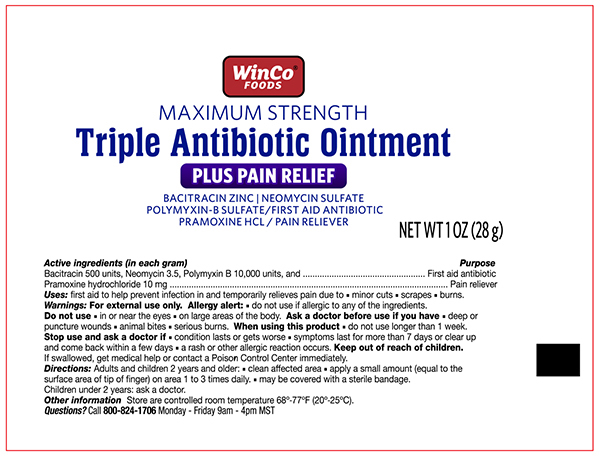 DRUG LABEL: WinCo Maximum Strength Triple Antibiotic
NDC: 67091-272 | Form: OINTMENT
Manufacturer: WinCo Foods, LLC
Category: otc | Type: HUMAN OTC DRUG LABEL
Date: 20241121

ACTIVE INGREDIENTS: BACITRACIN ZINC 500 [USP'U]/1 g; NEOMYCIN SULFATE 3.5 mg/1 g; POLYMYXIN B SULFATE 10000 [USP'U]/1 g; PRAMOXINE HYDROCHLORIDE 10 mg/1 g
INACTIVE INGREDIENTS: PETROLATUM

Winco Triple Antibiotic Plus Ointment 1 oz NBE Neosporin Plus

Active ingredients Purpose

Bacitracin zinc 500 units.............................................................................First aid antibiotic

Neomycin sulfate 3.5 mg............................................................................First aid antibiotic

Polymyxin B sulfate 10,000 units.................................................................First aid antibiotic

Pramoxine hydrochloride 10 mg..................................................................External analgesic

Uses

first aid to help prevent infection and for temporary relief of pain or discomfort in minor:

- cuts
- scrapes
- burns

Warnings

For external use only

Do not use

- if you are allergic to any of the ingredients
- in the eyes
- over large areas of the body

Ask a doctor before use if you have

- deep or puncture wounds
- animal bites
- serious burns

Stop use and ask a doctor if

- you need to use longer than 1 week
- the condition persists or gets worse
- symptoms persist for more than 1 week, or clear up and occur again within a few days
- rash or other allergic reaction develops

Keep out of reach of children.

If swallowed, get medical help or contact a Poison Control right away

Directions

- adults and children 2 years of age and older:
- clean the affected area
- apply a small amount of this product (an amount equal to the surface area of the tip of a finger) on the area 1 to 3 times daily
- may be covered with a sterile bandage
- children under 2 years of age: ask a doctor

Other information

- store between 20° to 25°C (68° to 77°F)
- Lot No. & Exp. Date: see box or see crimp of tube

Inactive Ingredients ;

petrolatum

DOSAGE AND ADMINISTRATION

DISTRIBUTED BY: WINCO FOODS, LLC, BOISE, ID 83704

Principle Display Panel -TUBE

WinCo Foods NDC 67091-272-28

Triple Antibiotic Plus Ointment

- Bacitracin Zinc
- Neomycin Sulfate
- Polymyxin B Sulfate
- Pramoxine HCL

NET WT 1 OZ (28g)

Principle Display Panel -CARTON

WinCo Foods NDC 67091-272-28

Triple Antibiotic Plus Ointment

- Bacitracin Zinc
- Neomycin Sulfate
- Polymyxin B Sulfate
- Pramoxine HCL

NET WT 1 OZ (28g)